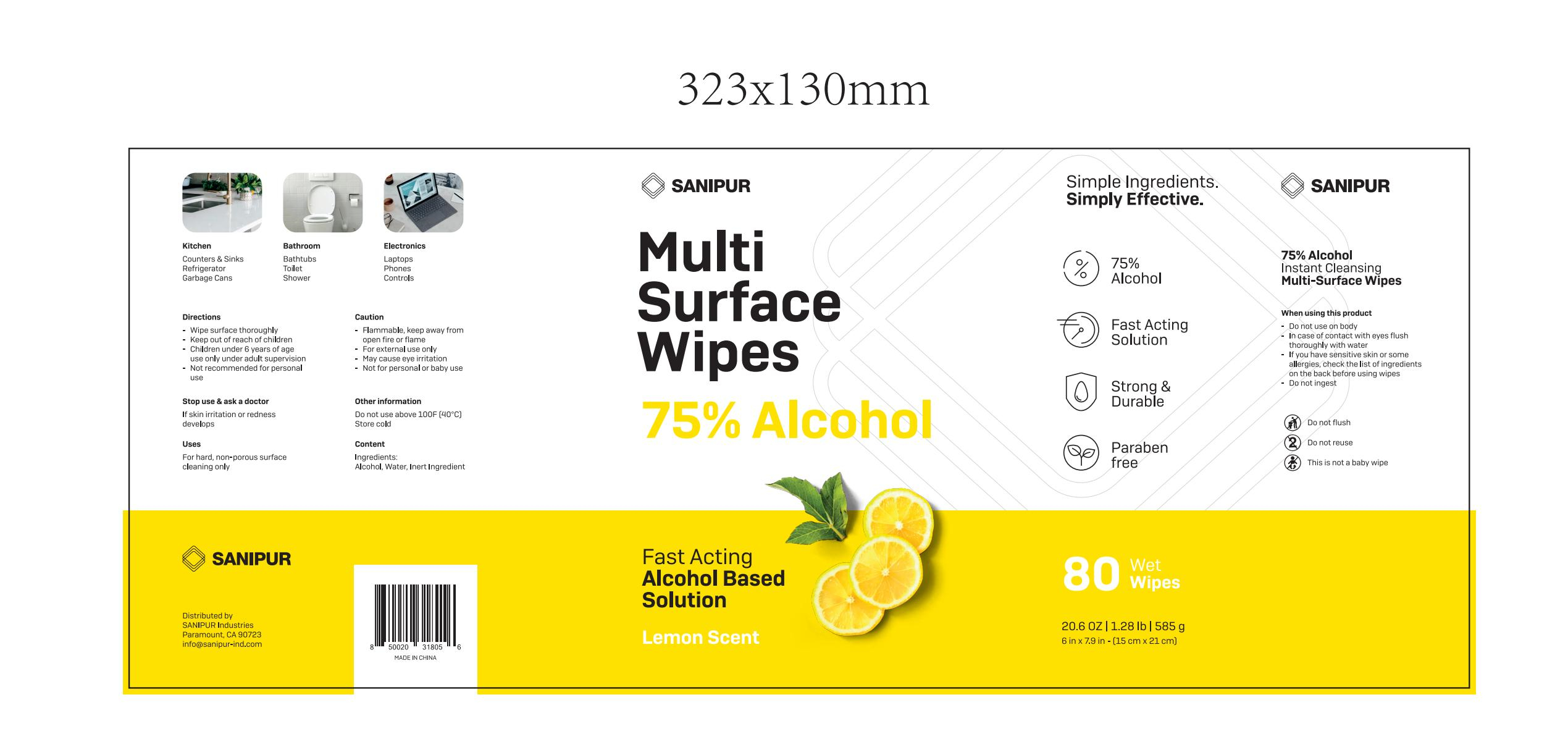 DRUG LABEL: Multi Surface Wipes 75%  Alcohol
NDC: 41546-011 | Form: CLOTH
Manufacturer: Zhejiang Huanghua Biological Technology Co., Ltd
Category: otc | Type: HUMAN OTC DRUG LABEL
Date: 20201022

ACTIVE INGREDIENTS: ALCOHOL 354.4 mL/80 1
INACTIVE INGREDIENTS: .ALPHA.-METHYLBENZYL ACETATE; LINALOOL, (+/-)-; CITRAL; WATER; GERANIOL

Do not use above 100F [4O°C]Store cold

INACTIVE INGREDIENT

Water

Linalool

Styrallyl acetate

Geraniol

Citral

INDICATIONS AND USAGE

Wipe surface thoroughly

ACTIVE INGREDIENT

Ethanol

Keep out of reach of children

PURPOSE

Disinfection
Sterilization
No Rinseing

WARNINGS

Flammable, keep away fromopen fire or flame.For external use only